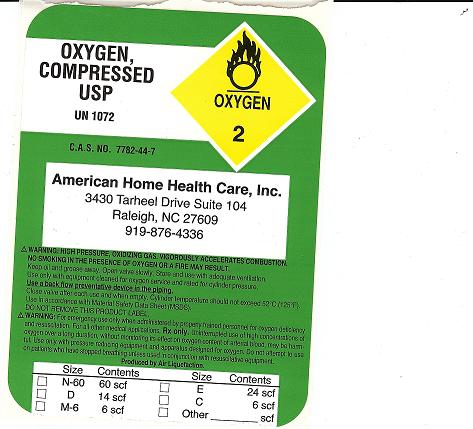 DRUG LABEL: Oxygen
NDC: 67361-001 | Form: GAS
Manufacturer: American Home Health Care, Inc.
Category: prescription | Type: HUMAN PRESCRIPTION DRUG LABEL
Date: 20100111

ACTIVE INGREDIENTS: Oxygen 210 mL/1 L

PACKAGE LABEL

OXYGEN, COMPRESSED USP